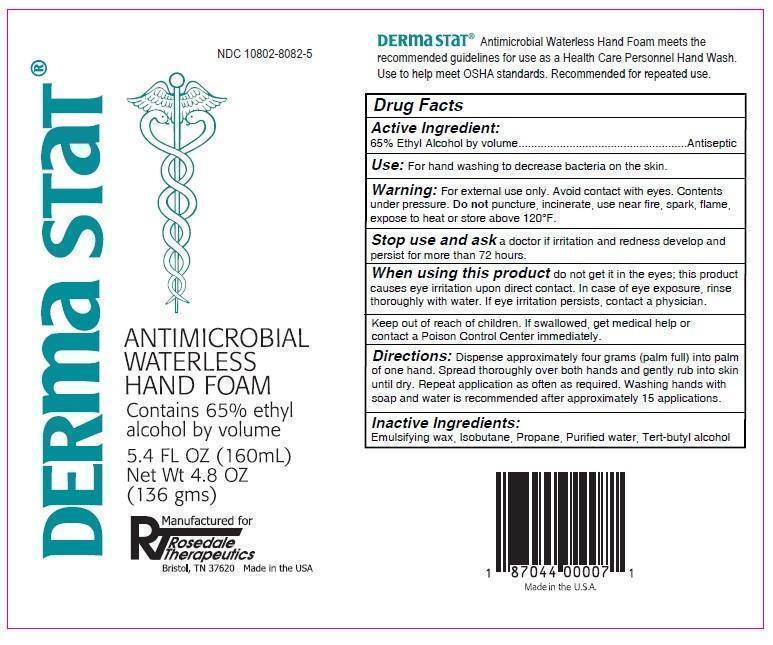 DRUG LABEL: Derma Stat
NDC: 10802-8082 | Form: AEROSOL, FOAM
Manufacturer: Rosedale Therapeutics, LLC
Category: otc | Type: HUMAN OTC DRUG LABEL
Date: 20150216

ACTIVE INGREDIENTS: ALCOHOL 65 mL/100 mL
INACTIVE INGREDIENTS: CETOSTEARYL ALCOHOL; POLYSORBATE 60; ISOBUTANE; PROPANE; WATER; TERT-BUTYL ALCOHOL

Derma Stat

Active Ingredient:

65% Ethyl Alcohol by volume

PURPOSE

Antiseptic

Keep out of reach of children. If swallowed, get medical help or contact a Poison Control Center immediately.

INDICATIONS AND USAGE

Use: For hand washing to decrease bacteria on the skin.

WARNINGS

Warning: For external use only. Avoid contact with eyes. Contents under pressure. Do not puncture incinerate, use near fire, spark, flame, expose to heat or store above 120°F.

Stop use and ask a doctor if irritation and redness develop and persist for more than 72 hours.

When using this product do not get it in the eyes; this product causes eye irritation upon direct contact. In case of eye exposure, rinse thoroughly with water. If eye irritation persists, contact a physician.

DOSAGE AND ADMINISTRATION

Directions: Dispense approximately four grams (palm full) into palm of one hand. Spread thoroughly over both hands and gently rub into skin until dry. Repeat application as often as required. Washing hands with soap and water is recommended after approximately 15 applications.

Inactive Ingredients:

Emulsifying wax, Isobutane, Propane, Purified water, Tert-butyl alcohol

DERMA STAT® Antimicrobial Waterless Hand Foam meets the recommended guidelines for use as a Health Care Personnel Hand Wash. Use to help meet OSHA standards. Recommended for repeated use.